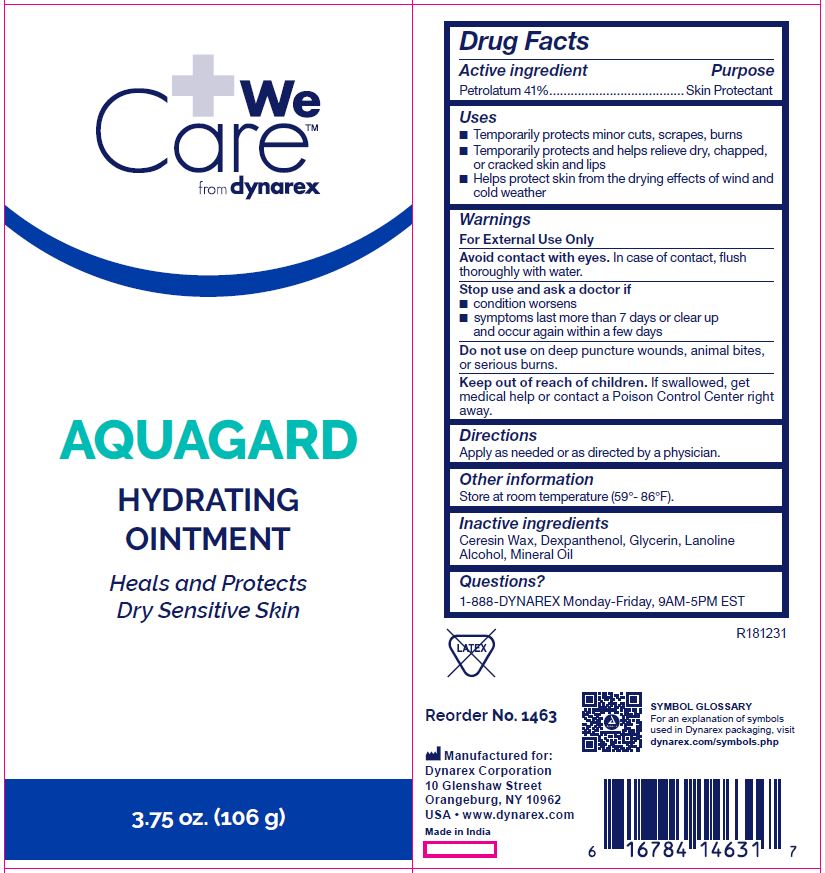 DRUG LABEL: AquaGard
NDC: 67777-146 | Form: OINTMENT
Manufacturer: Dynarex Corporation
Category: otc | Type: HUMAN OTC DRUG LABEL
Date: 20190109

ACTIVE INGREDIENTS: PETROLATUM 100 g/44.28 g
INACTIVE INGREDIENTS: MINERAL OIL; LANOLIN ALCOHOLS; PARAFFIN

1463 NDC 67777-146-30

Active Ingredient

Petrolatum 44.28%

Purpose

Skin Protectant

Uses

- Temporarily protects minor cuts, scrapes, burns
- Temporarily protects and helps relieve dry, chapped, or cracked skin and lips
- Helps protect skin from the drying effects of wind and cold weather

Warnings

For External Use Only

Avoid contact with eyes. In case of contact, flush thoroughly with water.

Stop use and ask a doctor if

- condition worsens
- symptoms last more than 7 days or clear up and occur again within a few days

Do not use

on deep puncture wounds, animal bites, or serious burns.

KEEP OUT OF REACH OF CHILDREN

If swallowed, get medical help or contact a Poison Control Center right away.

Directions

Apply as needed or as directed by a physician.

Other information

Store at room temperature (59° - 86°F)

Inactive ingredients

Ceresin Wax, Dexpanthenol, Glycerin, Lanolin Alcohol, Mineral Oil

Questions?

1-888-DYNAREX Monday-Friday, 9AM-5PM EST